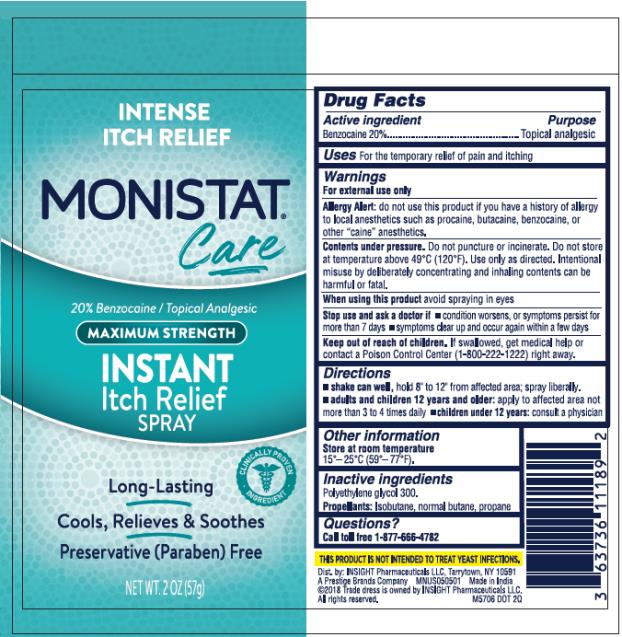 DRUG LABEL: Monistat Care Instant Itch Relief
NDC: 63736-050 | Form: SPRAY
Manufacturer: Insight Pharmaceuticals LLC
Category: otc | Type: HUMAN OTC DRUG LABEL
Date: 20241025

ACTIVE INGREDIENTS: BENZOCAINE 11.4 g/57 g
INACTIVE INGREDIENTS: POLYETHYLENE GLYCOL 300

Monistat Care Itch Relief Spray

Monistat Care – Benzocaine 20% / Topical analgesic

PDP

Monistat Care

20 % Benzocaine / Topical analgesic

Instant Itch Relief Spray

NET WT. 2 OZ (57 g)

Drug Facts

Active ingredient

Benzocaine 20%

Purpose

Topical analgesic

Uses

Temporary relief of pain and itching

Warnings

For external use only

Allergy alert: do not use this product if you have a history of allergy to local anesthetics such as procaine, butacaine, benzocaine or other "caine" anesthetics

Contents under pressure. Do not puncture or incinerate. Flammable mixture; do not use near fire or flame, or expose to heat or temperatures above 49°C (120°F). Use only as directed. Intentional misuse by deliberately concentrating and inhaling contents can be harmful or fatal.

When using this product

avoid contact with the eyes

Stop use and ask a doctor if

- condition worsens, or symptoms persists for more than 7 days
- symptoms clear up and occur again within a few days

Keep out of reach of children.

If swallowed, get medical help or contact a Poison Control Center (1-800-222-1222) right away.

Directions

- shake can well, hold 8" to 12" from affected area; spray liberally.
- adults and children 12 years and older: apply to affected area not more than 3 to 4 times daily
- children under 12 years: consult a physician

Other information

Store at room temperature 15°– 25°C (59°– 77°F).

Inactive ingredients

Polyethylene glycol 300
Propellant: Isobutane, normal butane, propane

Questions?

Call toll free 1-877-666-4782

PRINCIPAL DISPLAY PANEL

MONISTAT
Care
20% Benzocaine/ Tropical Analgesic
MAXIMUM STRENGTH
INSTANT
Itch Relief
SPRAY
Net WT.2 OZ(57g)